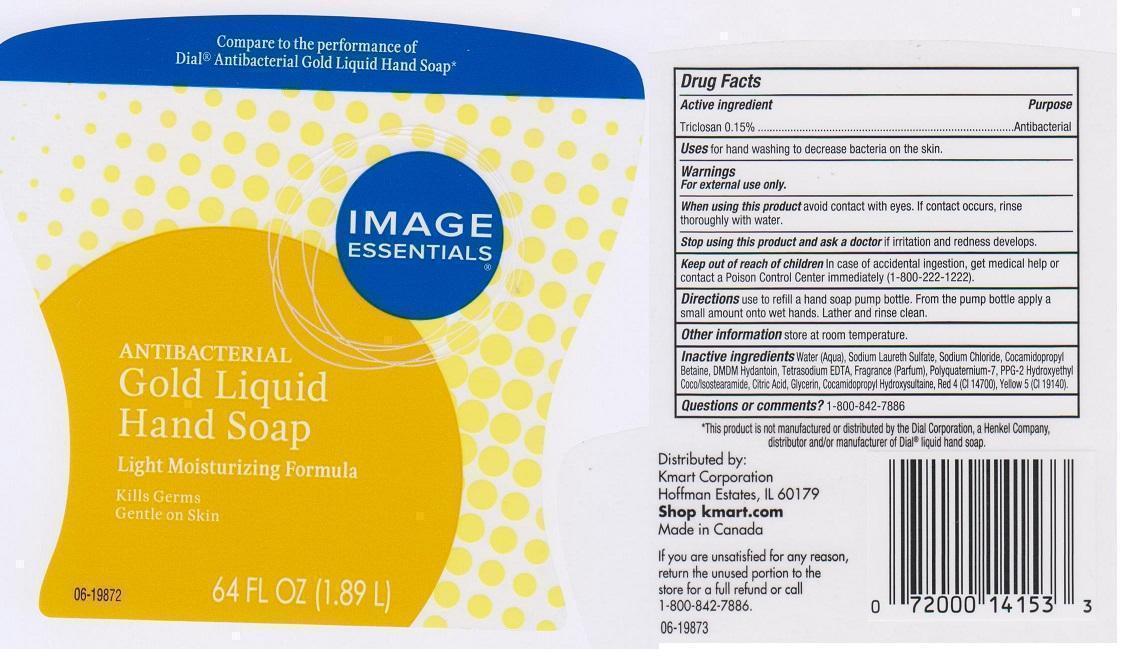 DRUG LABEL: IMAGE ESSENTIALS
NDC: 49738-722 | Form: LIQUID
Manufacturer: KMART CORPORATION
Category: otc | Type: HUMAN OTC DRUG LABEL
Date: 20141118

ACTIVE INGREDIENTS: TRICLOSAN 1.5 mg/1 mL
INACTIVE INGREDIENTS: WATER; SODIUM LAURETH SULFATE; SODIUM CHLORIDE; COCAMIDOPROPYL BETAINE; DMDM HYDANTOIN; EDETATE SODIUM; POLYQUATERNIUM-7 (70/30 ACRYLAMIDE/DADMAC; 1600000 MW); PPG-2 HYDROXYETHYL COCO/ISOSTEARAMIDE; CITRIC ACID MONOHYDRATE; GLYCERIN; COCAMIDOPROPYL HYDROXYSULTAINE; FD&C RED NO. 4; FD&C YELLOW NO. 5

DRUG FACTS

ACTIVE INGREDIENT

TRICLOSAN 0.15%

PURPOSE

ANTIBACTERIAL

USES

FOR HAND WASHING TO DECREASE BACTERIA ON THE SKIN

WARNINGS

FOR EXTERNAL USE ONLY

WHEN USING THIS PRODUCT

AVOID CONTACT WITH EYES. IF CONTACT OCCURS, RINSE THOROUGHLY WITH WATER

STOP USING THIS PRODUCT AND ASK A DCOTOR IF

IRRITATION AND REDNESS DEVELOPS

KEEP OUT OF REACH OF CHILDREN

IN CASE OF ACCIDENTAL INGESTION, GET MEDICAL HELP OR CONTACT A POISON CONTROL CENTER IMMEDIATELY (1-800-222-1222)

DIRECTIONS

USE TO REFILL A HAND SOAP PUMP BOTTLE. FROM THE PUMP BOTTLE APPLY A SMALL AMOUNT ONTO WET HANDS. LATHER AND RINSE CLEAN

OTHER INFORMATION

STORE AT ROOM TEMPERATURE

INACTIVE INGREDIENTS

WATER (AQUA), SODIUM LAURETH SULFATE, SODIUM CHLORIDE, COCAMIDOPROPYL BETAINE, DMDM HYDANTOIN, TETRASODIUM EDTA, FRAGRANCE (PARFUM), POLYQUATERNIUM-7, PPG-2 HYDROXYETHYL COCO/ISOSTEARAMIDE, CITRIC ACID, GLYCERIN, COCAMIDOPROPYL HYDROXYSULTAINE, RED 4 (CI 14700), YELLOW 5 (CI 19140)

QUESTIONS OR COMMENTS?

1-800-842-7886